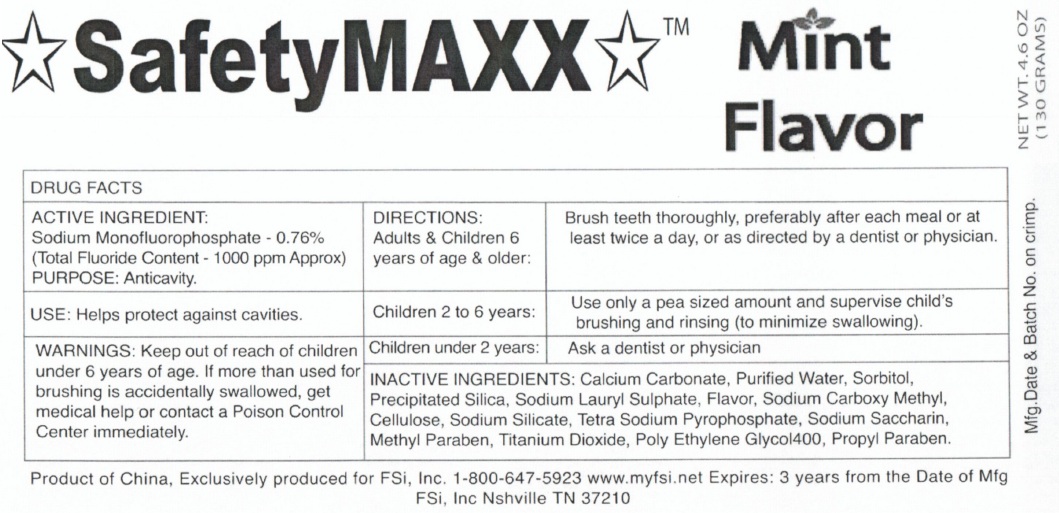 DRUG LABEL: SafetyMAXX Mint Flavor
NDC: 60371-339 | Form: PASTE, DENTIFRICE
Manufacturer: FSi, Inc.
Category: otc | Type: HUMAN OTC DRUG LABEL
Date: 20111115

ACTIVE INGREDIENTS: SODIUM MONOFLUOROPHOSPHATE 0.76 g/100 g
INACTIVE INGREDIENTS: CALCIUM CARBONATE; WATER; SORBITOL; SODIUM LAURYL SULFATE; CARBOXYMETHYLCELLULOSE SODIUM; SODIUM SILICATE; SODIUM PYROPHOSPHATE; SACCHARIN SODIUM DIHYDRATE; METHYLPARABEN; TITANIUM DIOXIDE; POLYETHYLENE GLYCOL 400; PROPYLPARABEN

SafetyMAXX Mint Flavor

Active Ingredient

Sodium Monofluorophosphate - 0.76% (Total fluoride content - 1000ppm Approx)

Purpose

Anticavity

Use:

Helps protect against cavities

Warnings

If more than used for brushing is swallowed, get medical help or contact a Poison Control Center immediately.

Keep out of reach of children under 6years of age.

Directions

Adults and children 6 years of age and older: Brush teeth thoroughly, preferably after each meal or at least twice a day, or as directed by a dentist.

Children 2 to 6 years: Use only a pea sized amount and supervise child's brushing and rinsing (to minimize swallowing)
Children under 2 years: ask a dentist or physician

Inactive Ingredients

Calcium carbonate, Purified Water, Sorbitol, Precipitated Silica, Sodium Lauryl Sulphate, Flavor, Sodium Carboxy Methyl Cellulose, Sodium Silicate, Tetra Sodium Pyrophosphate, Sodium Saccharin, methylparaben, Titanium Dioxide, Polyethylene Glycol 400 Propyl Paraben

Product of China, Exclusively produced for FSi, Inc. 1-800-647-5923 www.myfsi.net Expires 2 years from the DAte of Mfg

FSi, Inc Nashville TN 37210